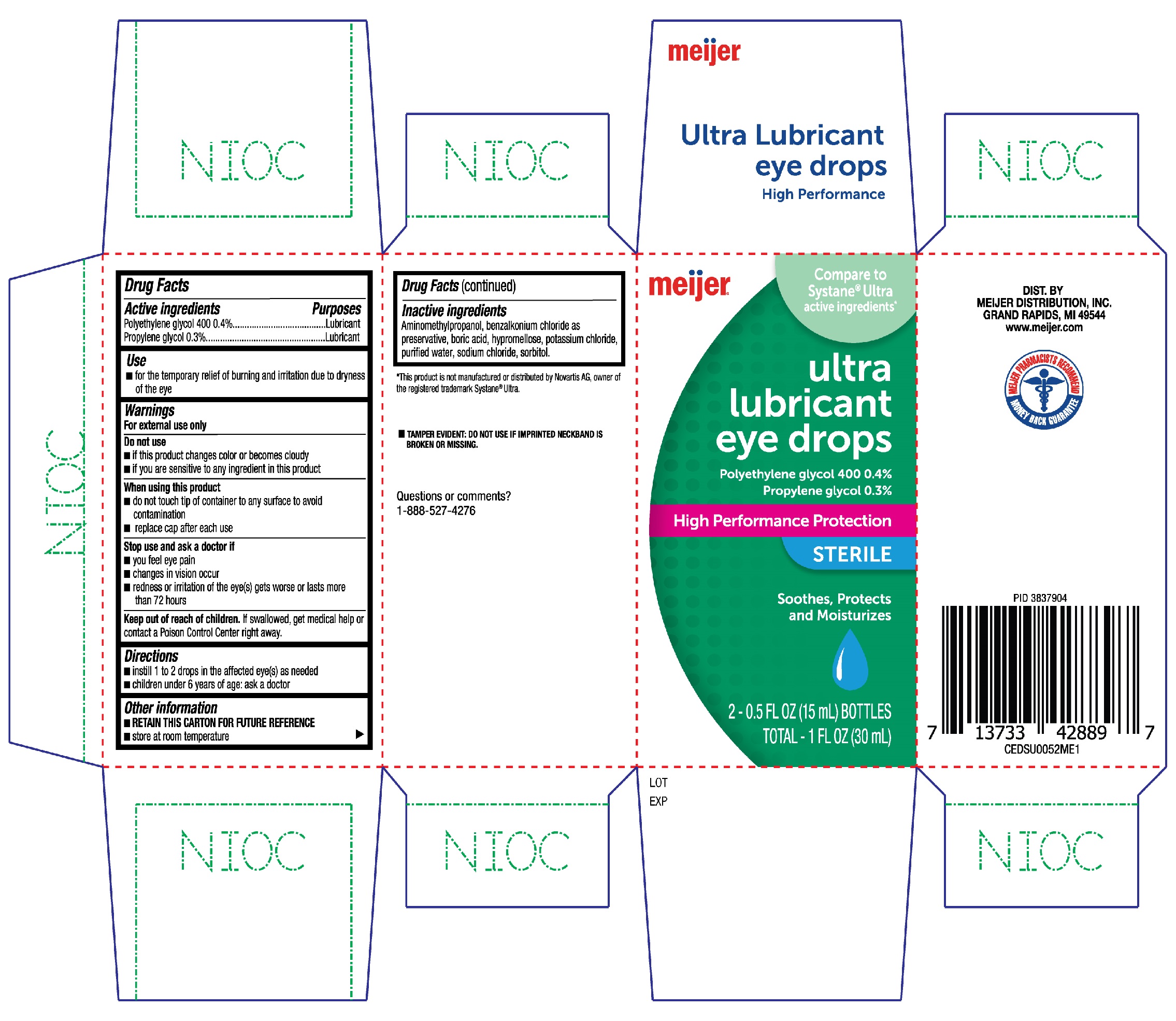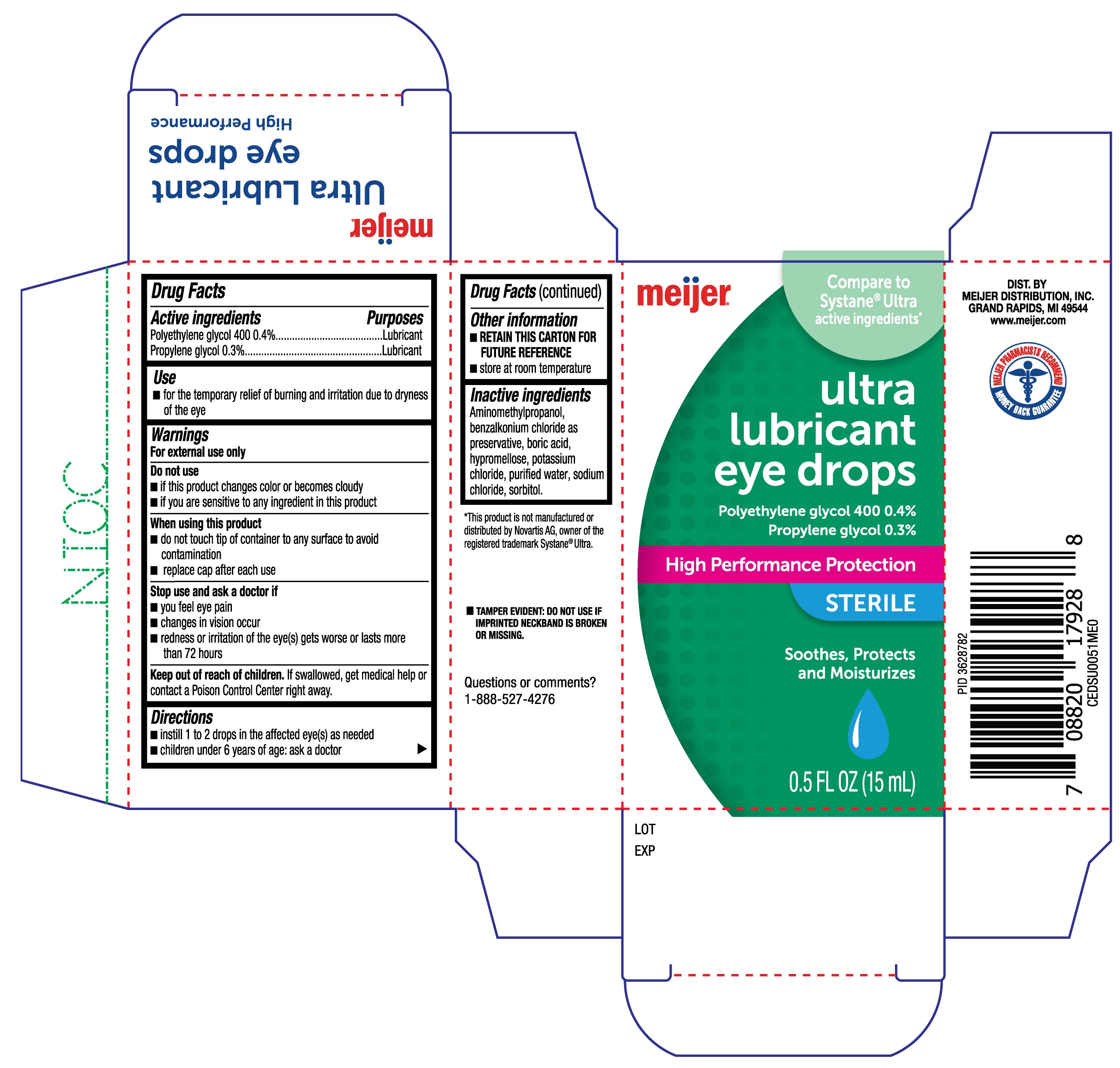 DRUG LABEL: Meijer Ultra Lubricant Eye Drops High Performance
NDC: 41250-937 | Form: SOLUTION/ DROPS
Manufacturer: Meijer Distribution, Inc.
Category: otc | Type: HUMAN OTC DRUG LABEL
Date: 20231222

ACTIVE INGREDIENTS: POLYETHYLENE GLYCOL 400 0.4 g/100 mL; PROPYLENE GLYCOL 0.3 g/100 mL
INACTIVE INGREDIENTS: SODIUM CHLORIDE; POTASSIUM CHLORIDE; HYPROMELLOSE, UNSPECIFIED; WATER; SORBITOL; AMINOMETHYLPROPANOL; BENZALKONIUM CHLORIDE; BORIC ACID

Meijer Ultra Lubricant Eye Drops High Performance 15mL and 15mL twin pk (PLD)

Active ingredients

Polyethylene glycol 400 0.4%

Propylene glycol 0.3%

Purposes

Lubricant

Lubricant

Use

- for the temporary relief of burning and irritation due to dryness of the eye

Warnings

For external use only

Do not use

- if this product changes color or becomes cloudy
- if you are sensative to any ingredient in this product

When using this product

- do not touch tip of container to any surface to avoid contamination
- replace cap after each use

Stop use and ask a doctor if

- you feel eye pain
- changes in vision occur
- redness or irritation of the eye(s) gets worse or lasts more than 72 hours

Keep out of reach of children.

If swallowed, get medical help or contact a Poison Control Center right away.

Directions

- instill 1 to 2 drops in the affected eye(s) as needed
- children under 6 years of age: ask a doctor

Other information

- RETAIN THIS CARTON FOR FUTURE REFERENCE
- store at room temperature

Inactive ingredients

Aminomethylpropanol, benzalkonium chloride as preservative, boric acid, hypromellose, potassium chloride, purified water, sodium chloride, sorbitol.